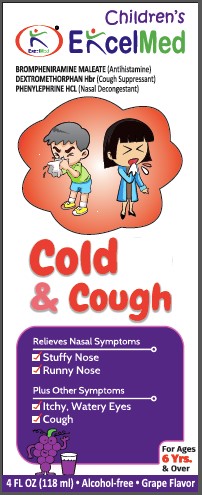 DRUG LABEL: Childrens Cough and Cold
NDC: 71027-047 | Form: LIQUID
Manufacturer: KINGSTON PHARMA LLC
Category: otc | Type: HUMAN OTC DRUG LABEL
Date: 20190130

ACTIVE INGREDIENTS: BROMPHENIRAMINE MALEATE 1 mg/5 mL; DEXTROMETHORPHAN HYDROBROMIDE 5 mg/5 mL; PHENYLEPHRINE HYDROCHLORIDE 2.5 mg/5 mL
INACTIVE INGREDIENTS: ANHYDROUS CITRIC ACID; FD&C BLUE NO. 1; FD&C RED NO. 40; GLYCERIN; PROPYLENE GLYCOL; WATER; SODIUM BENZOATE; SODIUM CITRATE; SORBITOL; SUCRALOSE

Children's Cough & Cold Liquid

Active Ingredient: Brompheniramine maleate 1 mg, Dextromethorphan HBr 5mg, Phenylephrine HCl 2.5 mg (in each 5 mL)

Purpose: Children's Cough & Cold

INDICATIONS AND USAGE

Cough & Cold

Warnings:

Do not use:

- If you are now taking a prescription monoamine oxidase inhibitor (MAOI) (certain drugs for depression, psychiatric, or emotional conditions or parkinson’s disease), or for 2 weeks after stopping the MAOI drug. If you do not know if your prescription drug contains an MAOI, ask a doctor or pharmacist before taking this product.
- To make a child sleep.

Ask a doctor before use if you have

- Glaucoma
- Thyroid disease
- High blood pressure
- Heart disease
- Diabetes
- Trouble urinating due to an enlarged prostate gland
- Persistent or chronic cough such as occurs with smoking, asthma or emphysema
- Cough that occurs with too much phlegm (mucus)
- A breathing problem such as emphysema or chronic bronchitis

Ask a doctor or pharmacist before use if you are

- Taking sedatives or tranquilizers

When using this product

- Do not exceed recommended dosage
- Excitability may occur especially in children
- Marked drowsiness may occur
- Avoid alcoholic drinks
- Alcohol, sedatives and tranquilizers may increase drowsiness
- Be careful when driving a motor vehicle or operating machinery

Stop use and ask doctor if

- Nervousness, dizziness or sleeplessness occur
- Symptoms do not get better within 7 days or are accompanied by fever
- Cough lasts more than 7 days, comes back, or occurs with fever, rash, or headache that lasts

A persistent cough may be a sign of a serious condition

KEEP OUT OF REACH OF CHILDREN

Keep this and all drugs out of the reach of children. In case of accidental overdose, seek professional assistance or contact a Poison control center right away.

PREGNANCY OR BREAST FEEDING

If pregnant or breast-feeding, ask a health professional before use.

Directions:

- Use enclosed dosing cup.
- Do not take more than 6 doses in any 24-hour period.
- Adults and children 12 years and over: take 4 teaspoons or 20 mL every 4-6 hours.
- Children 6 to under 12 years: take 2 teaspoons or 10 mL every 4-6 hours. ask a doctor
- Children 4 to under 6 years: do not use unless directed by a doctor
- Children under 4 years: do not use

STORAGE AND HANDLING

Store between 20°C to 25°C (68° to 77° F)

INACTIVE INGREDIENT

anhydrous citric acid, artificial flavor, FD&C blue no. 1, FD&C red no. 40, glycerin, propylene glycol, purified water, sodium benzoate, sodium citrate, sorbitol solution, sucralose

HOW SUPPLIED

(packs: 4oz) Kingston NDC# 71027-047-04